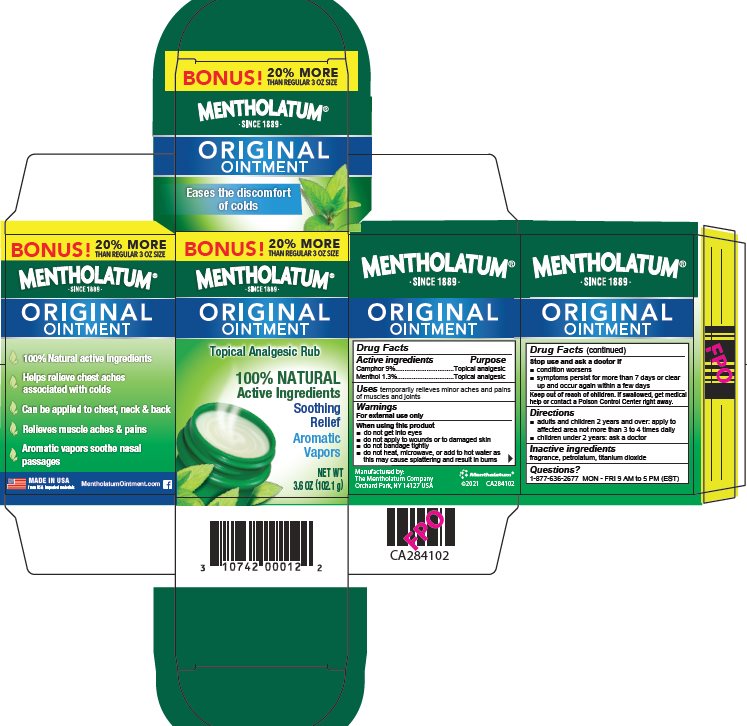 DRUG LABEL: Mentholatum
NDC: 10742-0002 | Form: OINTMENT
Manufacturer: The Mentholatum Company
Category: otc | Type: HUMAN OTC DRUG LABEL
Date: 20241213

ACTIVE INGREDIENTS: CAMPHOR (NATURAL) 90 mg/1 g; MENTHOL, UNSPECIFIED FORM 13 mg/1 g
INACTIVE INGREDIENTS: PETROLATUM; TITANIUM DIOXIDE

Drug Facts

Active ingredients

Camphor 9%

Menthol 1.3%

Purpose

Camphor - Topical Analgesic

Menthol - Topical Analgesic

Uses

temporarily relieves minor aches and pains of muscles and joints

Warnings

For external use only

When using this product

- do not get into eyes
- do not apply to wounds or to damaged skin
- do not bandage tightly
- do not heat, microwave, or add to hot water as this may cause splattering and result in burns

Stop use and ask a doctor if

- condition worsens
- symptoms persist for more than 7 days or clear up and occur again within a few days

Keep out of reach of children.

If swallowed, get medical help or contact a Poison Control Center right away.

Directions

- adults and children 2 years and over: apply to affected area not more than 3 to 4 times daily
- children under 2 years: ask a doctor

Inactive ingredients

fragrance, petrolatum, titanium dioxide

Questions?

1-877-636-2677 MON-FRI 9AM to 5PM (EST)